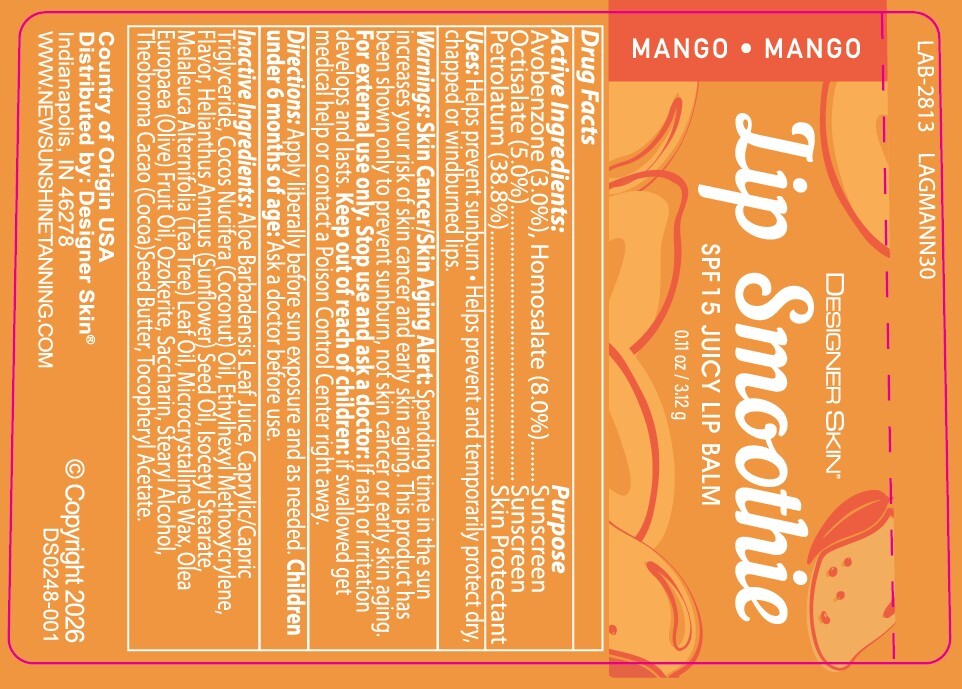 DRUG LABEL: Designer Lip Smoothie SPF 15 Lip Balm
NDC: 84061-127 | Form: STICK
Manufacturer: Australian Gold
Category: otc | Type: HUMAN OTC DRUG LABEL
Date: 20260122

ACTIVE INGREDIENTS: OCTISALATE 50 mg/1 g; AVOBENZONE 30 mg/1 g; PETROLATUM 388 mg/1 g; HOMOSALATE 80 mg/1 g
INACTIVE INGREDIENTS: CERESIN 165 mg/1 g; ISOCETYL STEARATE 23 mg/1 g; .ALPHA.-TOCOPHEROL ACETATE 5 mg/1 g

Drug Facts

Active ingredient

Avobenzone (3.0%), Homosalate (8.0%), Octisalate (5.0%)

Petrolatum (38.8%)

Purpose

Sunscreen, Sunscreen, Skin Protectant

Keep Out of Reach of Children

If swallowed get medical help or contact a Poison Control Center right away.

Uses

Helps prevent sunburn. Helps prevent and temporarily protect dry, chapped, or windburned lips.

Warnings

For external use only: When using this product. Keep out of eyes. Rinse with water to remove. Stop use and ask a doctor: if rash or irritation develops and lasts.

Directions

Apply liberally 15 minutes before sun exposure and as needed. Children under 6 months: Ask a doctor.

Inactive Ingredients

Aloe Barbadensis Leaf Juice, Caprylic/Capric Triglyceride, Cocos Nucifera (Coconut) Oil, Ethylhexyl Methoxycrylene, Flavor, Helianthus Annuus (Sunflower) Seed Oil, Isocetyl Stearate, Melaleuca Alternifolia (Tea Tree) Leaf Oil, Microcrystalline Wax, Olea Europaea (Olive) Fruit Oil, Ozokerite, Saccharin, Stearyl Alcohol, Theobroma Cacao (Cocoa) Seed Butter, Tocopheryl Acetate.